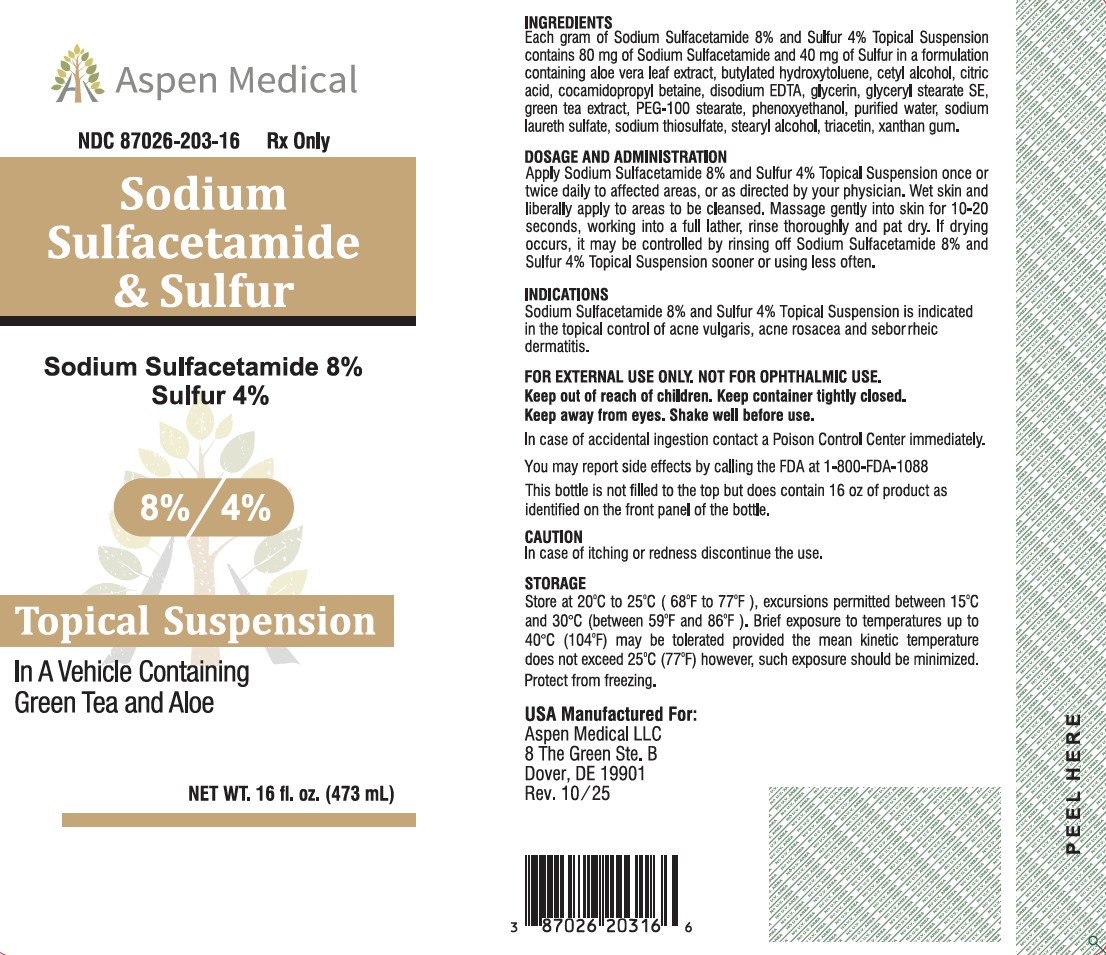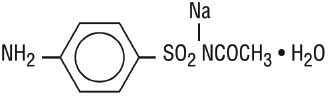 DRUG LABEL: SODIUM SULFACETAMIDE, SULFUR
NDC: 87026-203 | Form: LIQUID
Manufacturer: Aspen Medical LLC
Category: prescription | Type: HUMAN PRESCRIPTION DRUG LABEL
Date: 20260221

ACTIVE INGREDIENTS: SULFACETAMIDE SODIUM 80 mg/1 g; SULFUR 40 mg/1 g
INACTIVE INGREDIENTS: BUTYLATED HYDROXYTOLUENE; TRIACETIN; XANTHAN GUM; EDETATE DISODIUM; SODIUM THIOSULFATE; ALOE BARBADENSIS LEAF POWDER; GLYCERYL STEARATE SE; PHENOXYETHANOL; CETOSTEARYL ALCOHOL; COCAMIDOPROPYL BETAINE; WATER; CITRIC ACID; GLYCERIN; PEG-100 STEARATE; SODIUM LAURETH SULFATE; GREEN TEA LEAF

Sodium Sulfacetamide 8% Sulfur 4%

Rx Only

FOR EXTERNAL USE ONLY. NOT FOR OPHTHALMIC USE.
Keep out of reach of children. Keep container tightly closed.
Keep away from eyes. Shake well before use.

In case of accidental ingestion contact a Poison Control Center immediately.

You may report side effects by calling the FDA at 1-800-FDA-1088

INACTIVE INGREDIENT

Aloe vera leaf extract, butylated hydroxytoluene, cetyl alcohol, citric acid, cocamidopropyl betaine, disodium EDTA, glycerin, glyceryl stearate SE, green tea extract, PEG-100 stearate, phenoxyethanol, purified water, sodium laureth sulfate, sodium thiosulfate, stearyl alcohol, triacetin, xanthan gum.

INDICATIONS AND USAGE

Sodium Sulfacetamide 8% and Sulfur 4% Topical Suspension is indicated in the topical control of acne vulgaris, acne rosacea and seborrheic dermatitis.

CAUTION

In case of itching or redness discontinue the use.

DOSAGE AND ADMINISTRATION

Apply Sodium Sulfacetamide 8% and Sulfur 4% Topical Suspension once or twice daily to affected areas, or as directed by your physician. Wet skin and liberally apply to areas to be cleansed. Massage gently into skin for 10-20 seconds, working into a full lather, rinse thoroughly and pat dry. If drying occurs, it may be controlled by rinsing off Sodium Sulfacetamide 8% and Sulfur 4% Topical Suspension sooner or using less often.

STORAGE AND HANDLING

Store at 20℃ to 25C (68°F to 77°F), excursions permitted between 15C and 30C (between 59°F and 86°F). Brief exposure to temperatures up to 40C (104°F) may be tolerated provided the mean kinetic temperature does not exceed 25C (77°F) however, such exposure should be minimized. Protect from freezing.

In case of accidental ingestion contact a Poison Control Center immediately. Keep container tightly closed.

You may report side effects by calling the FDA at 1-800-FDA-1088

DESCRIPTION

Sodium sulfacetamide is a sulfonamide with antibacterial activity while sulfur acts as a keratolytic agent. Chemically sodium sulfacetamide is N-[(4-aminophenyl)sulfonyl]-acetamide monosodium salt, monohydrate. The structural formula is:

CONTRAINDICATIONS

This product is contraindicated for use by persons with known or suspected hypersensitivity to sulfonamides, sulfur or any other component of this preparation. This product is not to be used by patients with kidney disease.

CLINICAL PHARMACOLOGY

The most widely accepted mechanism of action of sulfonamides is the woods-fildes theory, which is based on the fact that sulfonamides act as competitive antagonists to para-aminobenzoic acid (PABA), an essential component for bacterial growth. While absorption through intact skin has not been determined, sodium sulfacetamide is readily absorbed from the gastrointestinal tract when taken orally and excreted in the urine, largely unchanged. The biological half-life has variously been reported as 7 to 12.8 hours. The exact mode of action of sulfur in the treatment of acne is not known, but it has been reported that it inhibits the growth of Propionibacterium acnes and the formation of free fatty acids.

WARNINGS

Although rare, sensitivity to sodium sulfacetamide may occur. Therefore, caution and careful supervision should be observed when prescribing this drug for patients who may be prone to hypersensitivity to topical sulfonamides. Systemic toxic reactions such as agranulocytosis, acute hemolytic anemia, purpura hemorrhagica, drug fever, jaundice and contact dermatitis indicate hypersensitivity to sulfonamides. Particular caution should be employed if areas of denuded or abraded skin are involved.

GENERAL

If irritation develops, use of the product should be discontinued and appropriate therapy instituted. Patients should be carefully observed for possible local irritation or sensitization during long-term therapy. The object of this therapy is to achieve desquamation without irritation, but sodium sulfacetamide and sulfur can cause reddening and scaling of the epidermis. These side effects are not unusual in the treatment of acne vulgaris, but patients should be cautioned about the possibility.

INFORMATION FOR PATIENTS

Avoid contact with eyes, eyelids, lips and mucous membranes, If accidental contact occurs, rinse with water. If excessive irritation develops, discontinue use and consult your physician.

CARCINOGENESIS & MUTAGENESIS & IMPAIRMENT OF FERTILITY

Long-term studies in animals have not been performed to evaluate carcinogenic potential.

PREGNANCY Category C

Animal reproduction studies have not been conducted with Sodium Sulfacetamide 8% and Sulfur 4% Topical Suspension. It is not known whether Sodium Sulfacetamide 8% and Sulfur 4% Topical Suspension can cause fetal harm when administered to a pregnant woman or can affect reproduction capacity. Sodium Sulfacetamide 8% and Sulfur 4% Topical Suspension should be given to a pregnant woman only if clearly needed.

NURSING MOTHERS

It is not known whether sodium sulfacetamide is excreted in the human milk following topical use of Sodium Sulfacetamide 8% and Sulfur 4% Topical Suspension. However, small amounts of orally administered sulfonamides have been reported to be eliminated in human milk. In view of this and because many drugs are excreted in human milk, caution should be exercised when Sodium Sulfacetamide 8% and Sulfur 4% Topical Suspension is administered to a nursing woman.

PEDIATRIC USE

Safety and effectiveness in children under the age of 12 have not been established.

ADVERSE REACTIONS

Although rare, sodium sulfacetamide may cause local irritation. Call your doctor for medical advice about side effects.

HOW SUPPLIED

Sodium Sulfacetamide 8% and Sulfur 4% Topical Suspension is available in
16 fl oz (473 mL) bottles NDC 87026-203-16

This bottle is not filled to the top but does contain 16 oz of product as identified on the front panel of the bottle.

USA Manufactured For:

Aspen Medical LLC

8 The Green Ste. B

Dover, DE 19901

Rev. 10/25

PACKAGE LABEL

Aspen Medical

NDC 87026-203-16

Rx Only

Sodium

Sulfacetamide

& Sulfur

Sodium Sulfacetamide 8%

Sulfur 4%

8%/4%

Topical Suspension

In A Vehicle Containing

Green Tea and Aloe

NET WT. 16 fl. oz. (473 mL)